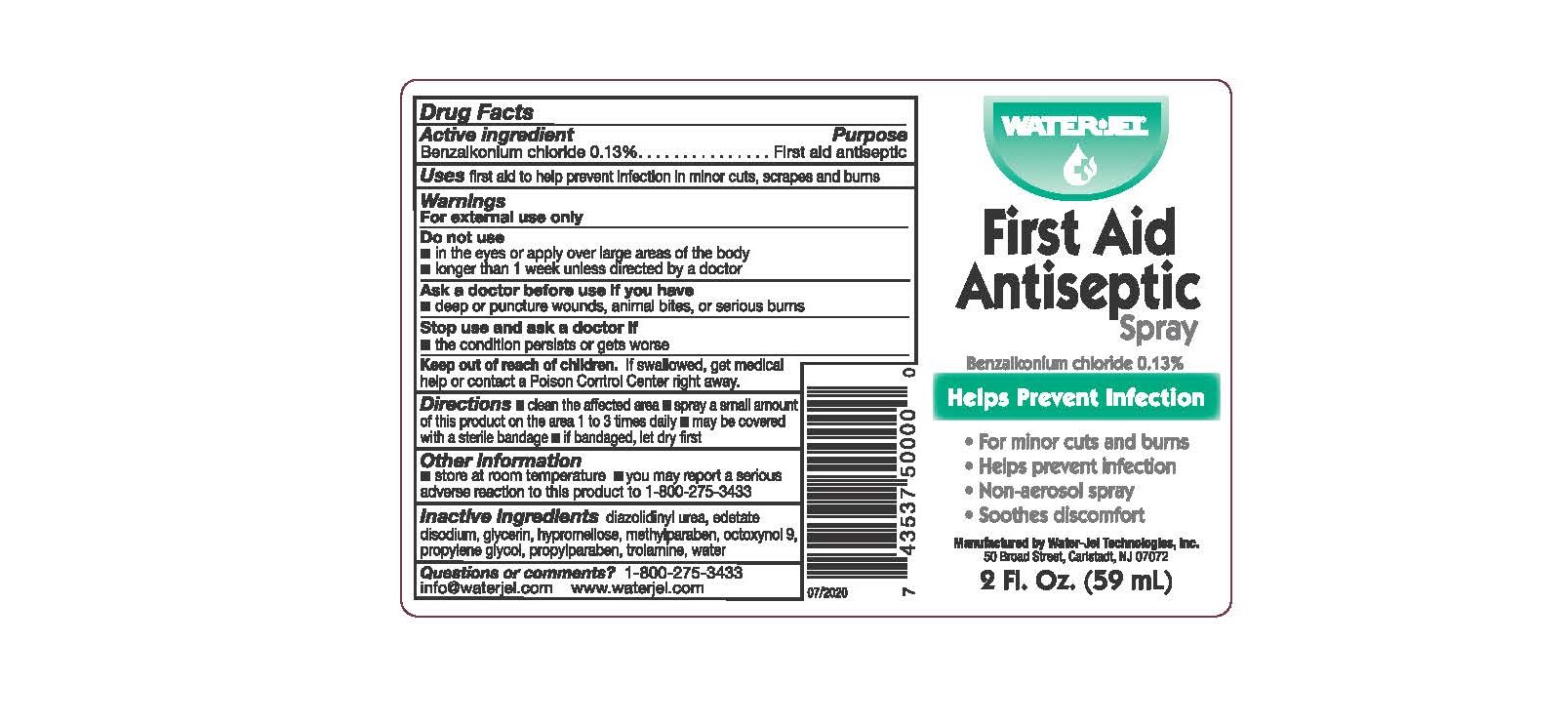 DRUG LABEL: First Aid Antiseptic
NDC: 59898-401 | Form: SPRAY
Manufacturer: Water-Jel Technologies
Category: otc | Type: HUMAN OTC DRUG LABEL
Date: 20250106

ACTIVE INGREDIENTS: BENZALKONIUM CHLORIDE 0.13 g/100 mL
INACTIVE INGREDIENTS: OCTOXYNOL 9; EDETATE DISODIUM; GLYCERIN; TROLAMINE; METHYLPARABEN; PROPYLENE GLYCOL; DIAZOLIDINYL UREA; WATER; HYPROMELLOSE 2208 (100000 MPA.S); PROPYLPARABEN

First Aid Antiseptic Spray

Active ingredient

Benzalkonium chloride 0.13%

Purpose

First aid antiseptic

Uses

first aid to help prevent infection in minor cuts, scrapes and burns

Warnings

For external use only

Do not use

- in the eyes or apply over large areas of the body
- longer than 1 week unless directed by a doctor

Ask a doctor before use if you have

- deep or puncture wounds, animal bites, or serious burns

Stop use and ask a doctor if

- the condition persists or gets worse

Keep out of the reach of children

If swallowed, get medical help or contact a Poison Control Center right away.

Directions

- clean the affected area
- spray a small amount of this product on the area 1 to 3 times daily
- may be covered with a sterile bandage
- if bandaged, let dry first

Other information

- shake well
- store at room temperature
- you may report a serious adverse reaction to this product to 1-800-275-3433

Inactive ingredients

diazolidinyl urea, edetate disodium, glycerin, hypromellose, methylparaben, octoxynol-9, propylene glycol, propylparaben, triethanolamine, water

Questions or comments?

1-800-275-3433 info@waterjel.com www.waterjel.com
Manufactered by Water-Jel Technologies, Inc., 50 Broad Street,
Carlstadt, NJ 07072, USA